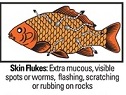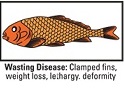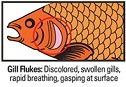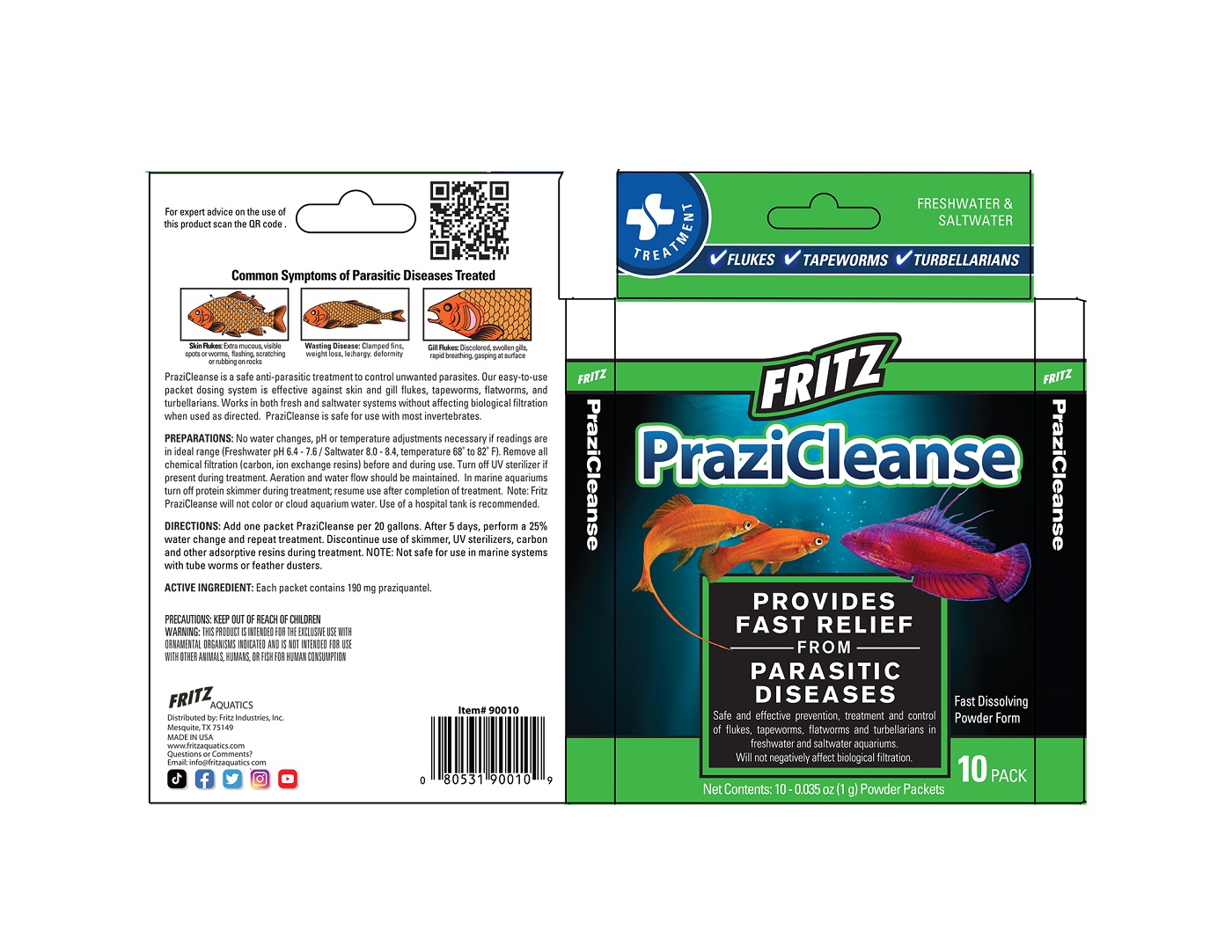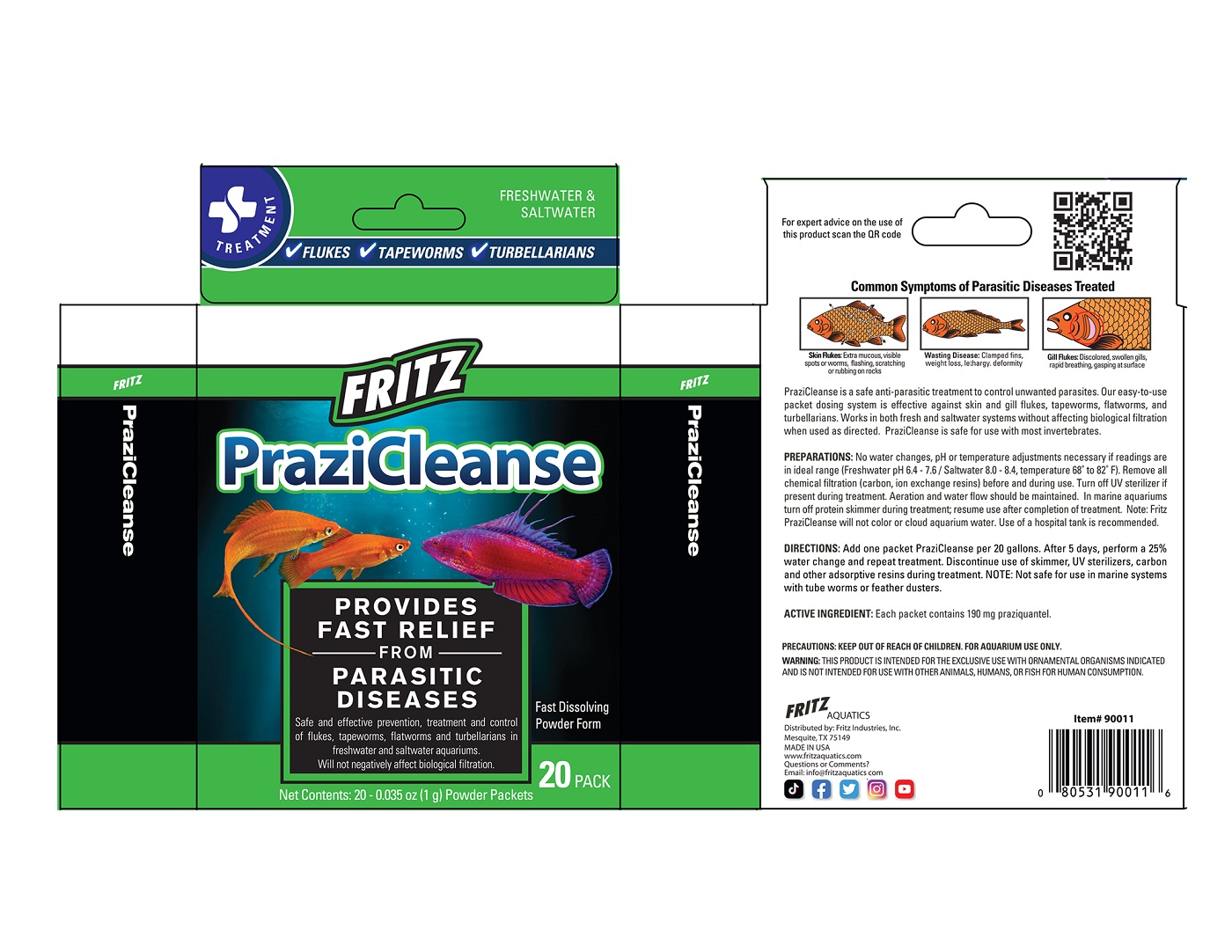 DRUG LABEL: PraziCleanse
NDC: 53745-017 | Form: POWDER
Manufacturer: Fritz Industries
Category: animal | Type: OTC ANIMAL DRUG LABEL
Date: 20211206

ACTIVE INGREDIENTS: praziquantel 190 mg/1 g
INACTIVE INGREDIENTS: SILICON DIOXIDE; DEXTROSE; MALTODEXTRIN

PraziCleanse

INDICATIONS AND USAGE

Common Symptoms of Parasitic Diseases Treated

Skin Flukes: Extra mucous, visible spots or worms, flashing, scratching or rubbing on rocks

Wasting Disease: Clamped fins, weight loss, lethargy, deformity

Gill Flukes: Discolored, swollen gills, rapid breathing, gasping at surface

PraziCleanse is a safe anti-parasitic treatment to control unwanted parasites. Our easy-to-use packet dosing system is effective against skin and gill flukes, tapeworms, flatworms, and turbellarians. Works in both fresh and saltwater systems without affecting biological filtration when used as directed. PraziCleanse is safe for use with most invertebrates.

PREPARATIONS:

No water changes, pH or temperature adjustments necessary if readings are in ideal range (Freshwater pH 6.4 - 7.6 / Saltwater 8.0 - 8.4, temperature 68° to 82° F). Remove all chemical filtration (carbon, ion exchange resins) before and during use. Turn off UV sterilizer if present during treatment. Aeration and water flow should be maintained. In marine aquariums turn off protein skimmer during treatment; resume use after completion of treatment. Note: Fritz PraziCleanse will not color or cloud aquarium water. Use of a hospital tank is recommended.

DIRECTIONS:

Add one packet PraziCleanse per 20 gallons. After 5 days, perform a 25% water change and repeat treatment. Discontinue use of skimmer, UV sterilizers, carbon and other adsorptive resins during treatment. NOTE: Not safe for use in marine systems with tube worms or feather dusters.

ACTIVE INGREDIENT:

Each packet contains 190 mg praziquantel.

PRECAUTIONS:

KEEP OUT OF REACH OF CHILDREN

WARNING:

THIS PRODUCT IS INTENDED FOR THE EXCLUSIVE USE WITH ORNAMENTAL ORGANISMS INDICATED AND IS NOT INTENDED FOR USE WITH OTHER ANIMALS, HUMANS, OR FISH FOR HUMAN CONSUMPTION

FRITZ

PraziCleanse

Provides Fast Relief from Parasitic Diseases

Safe and effective prevention, treatment and control of flukes, tapeworms, flatworms and turbellarians in freshwater and saltwater aquariums. Will not negatively affect biological filtration.

Net Contents: 10-0.035 oz (1g) Powder Packets

FRITZ AQUATICS
Distributed by: Fritz Industries, Inc.
Mesquite, TX 75149
MADE IN USA
www.fritzaquatics.com
Questions or Comments?
Email: info@fritzaquatics.com